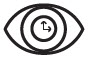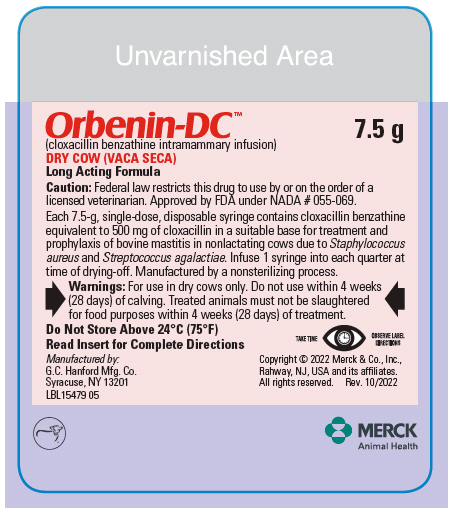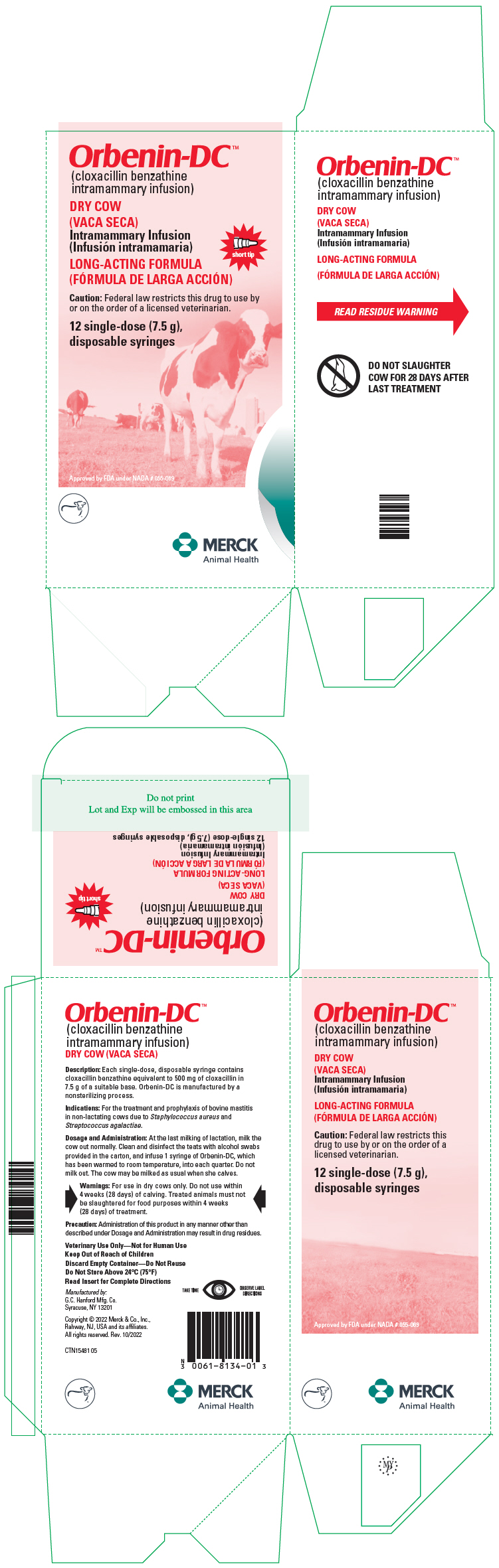 DRUG LABEL: Orbenin-DC
NDC: 0061-8134 | Form: SUSPENSION
Manufacturer: Merck Sharp & Dohme Corp.
Category: animal | Type: PRESCRIPTION ANIMAL DRUG LABEL
Date: 20241113

ACTIVE INGREDIENTS: CLOXACILLIN BENZATHINE 500 mg/7.5 mL

Orbenin-DC™
(cloxacillin benzathine
intramammary infusion)

CAUTION: Federal law restricts this drug to use by or on the order of a licensed veterinarian.

DESCRIPTION

DESCRIPTION: Orbenin-DC (cloxacillin benzathine intramammary infusion) is a stable, nonirritating suspension of cloxacillin benzathine containing the equivalent of 500 mg of cloxacillin per disposable syringe. Orbenin-DC is manufactured by a nonsterilizing process.

Cloxacillin benzathine is a semisynthetic penicillin derived from the penicillin nucleus, 6-amino-penicillanic acid. Cloxacillin benzathine is the benzathine salt of 6-[3-(2-chlorophenyl)-5-methylisoxazolyl-4-carboxamido] penicillanic acid.

The low solubility of Orbenin-DC results in an extended period of activity. Therefore, directions for use should be followed explicitly.

MECHANISM OF ACTION

ACTION: Cloxacillin benzathine is bactericidal in action against susceptible organisms during the stage of active multiplication. It acts through the inhibition of biosynthesis of cell wall mucopeptide. It is active against gram-positive organisms associated with mastitis such as Staphylococcus aureus and Streptococcus agalactiae and, because of its resistance to penicillinase, penicillin G-resistant staphylococci which may be the cause of mastitis.

Appropriate laboratory tests should be conducted, including in vitro culturing and susceptibility tests on pretreatment milk samples collected aseptically.

SUSCEPTIBILITY TEST: The Kirby-Bauer [Bauer AW, Kirby WMM, Sherris JC, et al: Antibiotic testing by a standardized single disk method, Am J Clin Path 45:493, 1966. Standardized Disk Susceptibility Test, Federal Register 37:20527–29, 1972.] procedure, utilizing antibiotic susceptibility disks, is a quantitative method that may be adapted to determining the sensitivity of bacteria in milk to Orbenin-DC.

For testing the effectiveness of Orbenin-DC in milk, follow the Kirby-Bauer procedure using the 1 mcg oxacillin susceptibility disk. Zone diameters for interpreting susceptibility are:

Resistant | Intermediate | Susceptible
≤ 10 mm | 11-12 mm | ≥ 13 mm

VETERINARY INDICATIONS

INDICATIONS: Orbenin-DC is indicated in the treatment and prophylaxis of bovine mastitis in nonlactating cows due to Staphylococcus aureus and Streptococcus agalactiae.

CONTRAINDICATIONS

CONTRAINDICATIONS: Because cloxacillin benzathine is relatively insoluble, Orbenin-DC's activity will be prolonged. Therefore, Orbenin-DC should not be used for the occasional cow which may have a dry period of less than 4 weeks. This precaution will avoid residues in the milk following removal of the colostrum.

WARNINGS

WARNINGS: For use in dry cows only. Do not use within 4 weeks (28 days) of calving. Treated animals must not be slaughtered for food purposes within 4 weeks (28 days) of treatment.

PRECAUTIONS

PRECAUTION: Because it is a derivative of 6-amino-penicillanic acid, Orbenin-DC has the potential for producing allergic reactions. Such reactions are rare; however, should they occur, the subject should be treated with the usual agents (antihistamines, pressor amines).

DOSAGE AND ADMINISTRATION: At the last milking of lactation, milk the cow out normally. Clean and disinfect the teats with alcohol swabs provided in the pail and infuse 1 syringe of Orbenin-DC, which has been warmed to room temperature, into each quarter. Do not milk out. The cow may be milked as usual when she calves.

The extent of subclinical and latent mastitis in a herd is frequently greater than suspected. In untreated herds a significant buildup of subclinical mastitis may occur during the dry period, which results in clinical severity after a few lactations. The adverse influence of subclinical mastitis on milk yield, the risk of cross-infection, and the chance of clinical mastitis flare-up make it necessary to treat the matter as a herd problem. Clinical studies have proven the value of treating all the cows in heavily infected herds as they are dried off. When the herd infection has been reduced, it may be desirable to be more selective in treating infected quarters.

Each pail contains 144 alcohol wipes to facilitate proper cleaning and disinfecting of the teat orifice.

HOW SUPPLIED

HOW SUPPLIED: Orbenin-DC is supplied in pails of 144 single dose syringes with 144 alcohol wipes. Each disposable syringe contains 500 mg of cloxacillin as the benzathine salt in 7.5 g of suitable base.

STORAGE AND HANDLING

Do Not Store Above 24°C (75°F)

Orbenin-DC™ is a trademark used by Intervet Inc.

Approved by FDA under NADA # 055-069

TAKE TIME |  | OBSERVE LABEL DIRECTIONS

Manufactured by: G.C. Hanford Mfg. Co.
Syracuse, NY 13201

© 2015-2021 Intervet Inc., a subsidiary of Merck & Co., Inc., Madison, NJ 07940, US
All rights reserved.
Rev. 08/2021

359106 R3
PAL16270 01

MERCK
Animal Health

PRINCIPAL DISPLAY PANEL - 7.5 g Syringe Label

Orbenin-DC™
(cloxacillin benzathine intramammary infusion)
7.5 g

DRY COW

Long Acting Formula

Caution: Federal law restricts this drug to use by or on the order of a
licensed veterinarian. Approved by FDA under NADA # 055-069.

PRINCIPAL DISPLAY PANEL - 7.5 g Syringe Carton

Orbenin-DC™
(cloxacillin benzathine
intramammary infusion)

DRY COW

Intramammary Infusion

short tip

LONG-ACTING FORMULA

Caution: Federal law restricts this drug to use by
or on the order of a licensed veterinarian.

12 single-dose (7.5 g),
disposable syringes

Approved by FDA under NADA # 055-069

MERCK
Animal Health